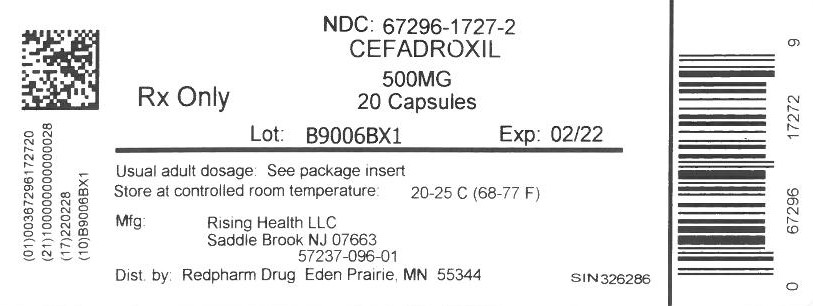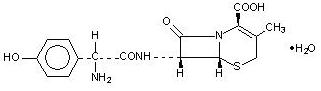 DRUG LABEL: Cefadroxil
NDC: 67296-1727 | Form: CAPSULE
Manufacturer: RedPharm Drug, Inc.
Category: prescription | Type: HUMAN PRESCRIPTION DRUG LABEL
Date: 20260123

ACTIVE INGREDIENTS: CEFADROXIL 500 mg/1 1
INACTIVE INGREDIENTS: LACTOSE MONOHYDRATE; MAGNESIUM STEARATE; FD&C BLUE NO. 1; D&C RED NO. 28; FD&C RED NO. 40; TITANIUM DIOXIDE; GELATIN, UNSPECIFIED; SODIUM LAURYL SULFATE; FERROSOFERRIC OXIDE

Cefadroxil 500mg

To reduce the development of drug-resistant bacteria and maintain the effectiveness of cefadroxil and other antibacterial drugs, cefadroxil should be used only to treat or prevent infections that are proven or strongly suspected to be caused by bacteria.

DESCRIPTION

Cefadroxil, USP is a semisynthetic cephalosporin antibiotic intended for oral administration. It is a white to yellowish-white crystalline powder. It is soluble in water and it is acid-stable. It is chemically designated as 5-Thia-1-azabicyclo[4.2.0]oct-2-ene-2-carboxylic acid, 7-[[amino(4-hydroxyphenyl)acetyl]amino]-3-methyl-8-oxo-, monohydrate, [6R-[6α,7β(R*)]]-. It has the formula C16H17N3O5S · H2O and the molecular weight of 381.40. It has the following structural formula:

Cefadroxil capsules contain the following inactive ingredients: Lactose monohydrate, magnesium stearate, FD&C Blue No.1, D&C Red No.28, FD&C Red No. 40, titanium dioxide, gelatin, sodium lauryl sulphate, and edible black ink (black iron oxide).

CLINICAL PHARMACOLOGY

Cefadroxil is rapidly absorbed after oral administration. Following single doses of 500 mg and 1000 mg, average peak serum concentrations were approximately 16 and 28 mcg/mL, respectively. Measurable levels were present 12 hours after administration. Over 90% of the drug is excreted unchanged in the urine within 24 hours. Peak urine concentrations are approximately 1800 mcg/mL during the period following a single 500 mg oral dose. Increases in dosage generally produce a proportionate increase in cefadroxil urinary concentration. The urine antibiotic concentration, following a 1 g dose, was maintained well above the MIC of susceptible urinary pathogens for 20 to 22 hours.

Microbiology

In vitro tests demonstrate that the cephalosporins are bactericidal because of their inhibition of cell-wall synthesis. Cefadroxil has been shown to be active against the following organisms both in vitro and in clinical infections (see INDICATIONS AND USAGE):
Beta-hemolytic streptococci
Staphylococci, including penicillinase-producing strains
Streptococcus (Diplococcus) pneumoniae
Escherichia coli
Proteus mirabilis
Klebsiella species
Moraxella (Branhamella) catarrhalis
Note: Most strains of Enterococcus faecalis (formerly Streptococcus faecalis) and Enterococcus faecium (formerly Streptococcus faecium) are resistant to cefadroxil. It is not active against most strains of Enterobacter species, Morganella morganii (formerly Proteus morganii), and P. vulgaris. It has no activity against Pseudomonas species and Acinetobacter calcoaceticus (formerly Mima and Herellea species).
Susceptibility Testing
For specific information regarding susceptibility test interpretive criteria and associated test methods and quality control standards recognized by FDA for this drug, please see: https://www.fda.gov/STIC.

INDICATIONS AND USAGE

Cefadroxil is indicated for the treatment of patients with infection caused by susceptible strains of the designated organisms in the following diseases:
Urinary tract infections caused by E. coli, P. mirabilis, and Klebsiella species.
Skin and skin structure infections caused by staphylococci and/or streptococci.
Pharyngitis and/or tonsillitis caused by Streptococcus pyogenes (Group A beta-hemolytic streptococci).
Note: Only penicillin by the intramuscular route of administration has been shown to be effective in the prophylaxis of rheumatic fever. Cefadroxil is generally effective in the eradication of streptococci from the oropharynx. However, data establishing the efficacy of cefadroxil for the prophylaxis of subsequent rheumatic fever are not available.
Note: Culture and susceptibility tests should be initiated prior to and during therapy. Renal function studies should be performed when indicated.
To reduce the development of drug-resistant bacteria and maintain the effectiveness of cefadroxil and other antibacterial drugs, cefadroxil should be used only to treat or prevent infections that are proven or strongly suspected to be caused by susceptible bacteria. When culture and susceptibility information are available, they should be considered in selecting or modifying antibacterial therapy. In the absence of such data, local epidemology and susceptibility patterns may contribute to the empiric selection of therapy.

CONTRAINDICATIONS

Cefadroxil is contraindicated in patients with known allergy to the cephalosporin group of antibiotics.

WARNINGS

BEFORE THERAPY WITH CEFADROXIL IS INSTITUTED, CAREFUL INQUIRY SHOULD BE MADE TO DETERMINE WHETHER THE PATIENT HAS HAD PREVIOUS HYPERSENSITIVITY REACTIONS TO CEFADROXIL, CEPHALOSPORINS, PENICILLINS, OR OTHER DRUGS. IF THIS PRODUCT IS TO BE GIVEN TO PENICILLIN-SENSITIVE PATIENTS, CAUTION SHOULD BE EXERCISED BECAUSE CROSS-SENSITIVITY AMONG BETA-LACTAM ANTIBIOTICS HAS BEEN CLEARLY DOCUMENTED AND MAY OCCUR IN UP TO 10% OF PATIENTS WITH A HISTORY OF PENICILLIN ALLERGY.
IF AN ALLERGIC REACTION TO CEFADROXIL OCCURS, DISCONTINUE THE DRUG. SERIOUS ACUTE HYPERSENSITIVITY REACTIONS MAY REQUIRE TREATMENT WITH EPINEPHRINE AND OTHER EMERGENCY MEASURES, INCLUDING OXYGEN, INTRAVENOUS FLUIDS, INTRAVENOUS ANTIHISTAMINES, CORTICOSTEROIDS, PRESSOR AMINES, AND AIRWAY MANAGEMENT, AS CLINICALLY INDICATED.
Clostridium difficile associated diarrhea (CDAD) has been reported with use of nearly all antibacterial agents, including cefadroxil, and may range in severity from mild diarrhea to fatal colitis. Treatment with antibacterial agents alters the normal flora of the colon leading to overgrowth of C. difficile.
C. difficile produces toxins A and B which contribute to the development of CDAD. Hypertoxin producing strains of C. difficile cause increased morbidity and mortality, as these infections can be refractory to antimicrobial therapy and may require colectomy. CDAD must be considered in all patients who present with diarrhea following antibiotic use. Careful medical history is necessary since CDAD has been reported to occur over two months after the administration of antibacterial agents.
If CDAD is suspected or confirmed, ongoing antibiotic use not directed against C. difficile may need to be discontinued. Appropriate fluid and electrolyte management, protein supplementation, antibiotic treatment of C. difficile, and surgical evaluation should be instituted as clinically indicated.

PRECAUTIONS

General

Cefadroxil should be used with caution in the presence of markedly impaired renal function (creatinine clearance rate of less than 50 mL/min/1.73 m^2). (See DOSAGE AND ADMINISTRATION.) In patients with known or suspected renal impairment, careful clinical observation and appropriate laboratory studies should be made prior to and during therapy.
Prescribing cefadroxil in the absence of a proven or strongly suspected bacterial infection or a prophylactic indication is unlikely to provide benefit to the patient and increases the risk of the development of drug-resistant bacteria.
Prolonged use of cefadroxil may result in the overgrowth of nonsusceptible organisms. Careful observation of the patient is essential. If superinfection occurs during therapy, appropriate measures should be taken.
Cefadroxil should be prescribed with caution in individuals with history of gastrointestinal disease particularly colitis.

Information for Patients

Patients should be counseled that antibacterial drugs including cefadroxil should only be used to treat bacterial infections. They do not treat viral infections (e.g., the common cold). When cefadroxil is prescribed to treat a bacterial infection, patients should be told that although it is common to feel better early in the course of therapy, the medication should be taken exactly as directed. Skipping doses or not completing the full course of therapy may (1) decrease the effectiveness of the immediate treatment and (2) increase the likelihood that bacteria will develop resistance and will not be treatable by cefadroxil or other antibacterial drugs in the future.
Diarrhea is a common problem caused by antibiotics which usually ends when the antibiotic is discontinued. Sometimes after starting treatment with antibiotics, patients can develop watery and bloody stools (with or without stomach cramps and fever) even as late as two or more months after having taken the last dose of the antibiotic. If this occurs, patients should contact their physician as soon as possible.

Drug/Laboratory Test Interactions

Positive direct Coombs’ tests have been reported during treatment with the cephalosporin antibiotics. In hematologic studies or in transfusion cross-matching procedures when antiglobulin tests are performed on the minor side or in Coombs’ testing of newborns whose mothers have received cephalosporin antibiotics before parturition, it should be recognized that a positive Coombs’ test may be due to the drug.

Carcinogenesis, Mutagenesis, Impairment of Fertility

No long-term studies have been performed to determine carcinogenic potential. No genetic toxicity tests have been performed.

Pregnancy

Pregnancy Category B
Reproduction studies have been performed in mice and rats at doses up to 11 times the human dose and have revealed no evidence of impaired fertility or harm to the fetus due to cefadroxil monohydrate. There are, however, no adequate and well controlled studies in pregnant women. Because animal reproduction studies are not always predictive of human response, this drug should be used during pregnancy only if clearly needed.

Labor and Delivery

Cefadroxil has not been studied for use during labor and delivery. Treatment should only be given if clearly needed.

Nursing Mothers

Caution should be exercised when cefadroxil monohydrate is administered to a nursing mother.

Pediatric Use

(See DOSAGE AND ADMINISTRATION.)

Geriatric Use

Of approximately 650 patients who received cefadroxil for the treatment of urinary tract infections in three clinical trials, 28% were 60 years and older, while 16% were 70 years and older. Of approximately 1000 patients who received cefadroxil for the treatment of skin and skin structure infection in 14 clinical trials, 12% were 60 years and older while 4% were 70 years and over. No overall differences in safety were observed between the elderly patients in these studies and younger patients. Clinical studies of cefadroxil for the treatment of pharyngitis or tonsillitis did not include sufficient numbers of patients 65 years and older to determine whether they respond differently from younger patients. Other reported clinical experience with cefadroxil has not identified differences in responses between elderly and younger patients, but greater sensitivity of some older individuals cannot be ruled out.
Cefadroxil is substantially excreted by the kidney, and dosage adjustment is indicated for patients with renal impairment (see DOSAGE AND ADMINISTRATION: Renal Impairment). Because elderly patients are more likely to have decreased renal function, care should be taken in dose selection, and it may be useful to monitor renal function.

ADVERSE REACTIONS

Gastrointestinal

Onset of pseudomembranous colitis symptoms may occur during or after antibiotic treatment (see WARNINGS). Dyspepsia, nausea and vomiting have been reported rarely. Diarrhea has also occurred.

Hypersensitivity

Allergies (in the form of rash, urticaria, angioedema, and pruritus) have been observed. These reactions usually subsided upon discontinuation of the drug. Anaphylaxis has also been reported.

Other

Other reactions have included hepatic dysfunction including cholestasis and elevations in serum transaminase, genital pruritus, genital moniliasis, vaginitis, moderate transient neutropenia, fever. Agranulocytosis, thrombocytopenia, idiosyncratic hepatic failure, erythema multiforme, Stevens-Johnson syndrome, serum sickness, and arthralgia have been rarely reported.
In addition to the adverse reactions listed above which have been observed in patients treated with cefadroxil, the following adverse reactions and altered laboratory tests have been reported for cephalosporin-class antibiotics:
Toxic epidermal necrolysis, abdominal pain, superinfection, renal dysfunction, toxic nephropathy, aplastic anemia, hemolytic anemia, hemorrhage, prolonged prothrombin time, positive Coombs’ test, increased BUN, increased creatinine, elevated alkaline phosphatase, elevated aspartate aminotransferase (AST), elevated alanine aminotransferase (ALT), elevated bilirubin, elevated LDH, eosinophilia, pancytopenia, neutropenia.
Several cephalosporins have been implicated in triggering seizures, particularly in patients with renal impairment, when the dosage was not reduced (see DOSAGE AND ADMINISTRATION and OVERDOSAGE). If seizures associated with drug therapy occur, the drug should be discontinued. Anticonvulsant therapy can be given if clinically indicated.

OVERDOSAGE

A study of children under six years of age suggested that ingestion of less than 250 mg/kg of cephalosporins is not associated with significant outcomes. No action is required other than general support and observation. For amounts greater than 250 mg/kg, induce gastric emptying.
In five anuric patients, it was demonstrated that an average of 63% of a 1 g oral dose is extracted from the body during a 6 to 8 hour hemodialysis session.

DOSAGE AND ADMINISTRATION

Cefadroxil is acid-stable and may be administered orally without regard to meals. Administration with food may be helpful in diminishing potential gastrointestinal complaints occasionally associated with oral cephalosporin therapy.

Adults

Urinary Tract Infections: For uncomplicated lower urinary tract infections (i.e., cystitis) the usual dosage is 1 or 2 g per day in a single (q.d.) or divided doses (b.i.d.).
For all other urinary tract infections the usual dosage is 2 g per day in divided doses (b.i.d.).
Skin and Skin Structure Infections: For skin and skin structure infections the usual dosage is 1 g per day in single (q.d.) or divided doses (b.i.d.).
Pharyngitis and Tonsillitis: Treatment of group A beta-hemolytic streptococcal pharyngitis and tonsillitis—1 g per day in single (q.d.) or divided doses (b.i.d.) for 10 days.

Children

For urinary tract infections, the recommended daily dosage for children is 30 mg/kg/day in divided doses every 12 hours. For pharyngitis, tonsillitis, and impetigo, the recommended daily dosage for children is 30 mg/kg/day in a single dose or in equally divided doses every 12 hours. For other skin and skin structure infections, the recommended daily dosage is 30 mg/kg/day in equally divided doses every 12 hours. In the treatment of beta-hemolytic streptococcal infections, a therapeutic dosage of cefadroxil should be administered for at least 10 days.

Renal Impairment

In patients with renal impairment, the dosage of cefadroxil should be adjusted according to creatinine clearance rates to prevent drug accumulation. The following schedule is suggested. In adults, the initial dose is 1000 mg of cefadroxil and the maintenance dose (based on the creatinine clearance rate [mL/min/1.73 m^2]) is 500 mg at the time intervals listed below.

Creatinine Clearances | Dosage Interval
0 to 10 mL/min | 36 hours
10 to 25 mL/min | 24 hours
25 to 50 mL/min | 12 hours

Patients with creatinine clearance rates over 50 mL/min may be treated as if they were patients having normal renal function.

HOW SUPPLIED

Cefadroxil Capsules, USP 500 mg are maroon/white colored, size “0” hard gelatin capsules filled with white to off-white granular free flowing powder and imprinted with “C” on maroon opaque cap and “97” on white opaque body with black ink.
Bottles of 50 NDC 57237-096-50
Bottles of 100 NDC 57237-096-01
Store at 20° to 25°C (68° to 77°F); excursions permitted to 15° to 30°C (59° to 86°F) [see USP Controlled Room Temperature].

Distributed by:
Rising Health, LLC
Saddle Brook, NJ 07663
Made in India
Code: TS/DRUGS/78/1996
Revised: 09/2018